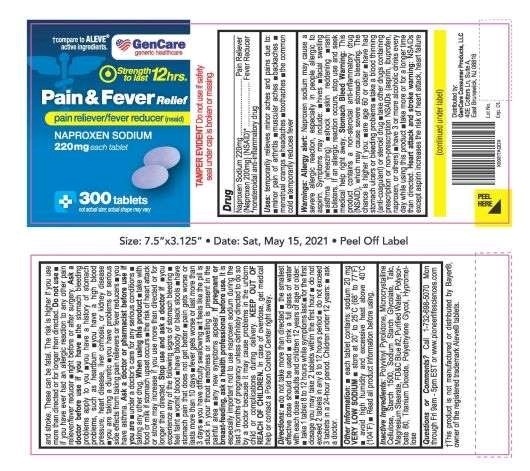 DRUG LABEL: Pain and Fever Relief
NDC: 72090-003 | Form: TABLET
Manufacturer: Pioneer Life Sciences, LLC
Category: otc | Type: HUMAN OTC DRUG LABEL
Date: 20210518

ACTIVE INGREDIENTS: NAPROXEN SODIUM 220 mg/1 1
INACTIVE INGREDIENTS: POLYSORBATE 80; POLYETHYLENE GLYCOL, UNSPECIFIED; POVIDONE, UNSPECIFIED; TALC; MICROCRYSTALLINE CELLULOSE; HYPROMELLOSE, UNSPECIFIED; STARCH, CORN; TITANIUM DIOXIDE; SODIUM STARCH GLYCOLATE TYPE A POTATO; FD&C BLUE NO. 2; MAGNESIUM STEARATE; WATER

Active Ingredient

Naproxen sodium 220mg
(naproxen 200mg) (NSAID)*
*nonsteroidal anti-inflammatory drug

Purpose

Pain reliever/Fever reducer

Uses:

temporarily relieves minor aches and pains due to:

■ minor pain of arthritis ■ muscular aches
■ backache ■ menstrual cramps
■ headache ■ toothache
■ the common cold
■ temporarily reduces fever

Warnings:

Allergy alert: Naproxen sodium may cause a severe
allergic reaction, especially in people allergic to aspirin.
Symptoms may include:
■ hives ■ facial swelling
■ asthma (wheezing) ■ shock ■ skin reddening
■ rash ■ blisters
If an allergic reaction occurs, stop use and seek medical
help right away.
Stomach bleeding warning: This product contains an
NSAID, which may cause severe stomach bleeding.
The chance is higher if you:
■ are age 60 or older
■ have had stomach ulcers or bleeding problems
■ take a blood thinning (anticoagulant) or steroid drug
■ take other drugs containing prescription or
nonprescription NSAIDs (aspirin, ibuprofen, naproxen,
or others)
■ have 3 or more alcoholic drinks every day while using
this product
■ take more or for a longer time than directed.
Heart attack and stroke warning: NSAIDs, except aspirin,
increase the risk of heart attack, heart failure and stroke.
These can be fatal. The risk is higher if you use more than
directed or for longer than directed.

Ask Doctor:

■ the stomach bleeding warning applies to you
■ you have a history of stomach problems, such as
heartburn
■ you have high blood pressure, heart disease, liver
cirrhosis, kidney disease, asthma, or had a stroke
■ you are taking a diuretic
■ you have problems or serious side effects from
taking pain relievers or fever reducers

ASK DOCTOR/PHARMACIST:

■ under a doctor's care for any serious condition
■ taking any other drug

STOP USE AND ASK A DOCTOR IF

■ you experience any of the
following signs of stomach bleeding:
■ feel faint
■ vomit blood ■ have bloody or black stools
■ have stomach pain that does not get better
■ you have symptoms of heart problems or stroke:
■ chest pain ■ trouble breathing
■ weakness in one part or side of body
■ slurred speech ■ leg swelling
■ pain gets worse or lasts more than 10 days
■ fever gets worse or lasts more than 3 days
■ you have difficulty swallowing
■ it feels like the pill is stuck in your throat
■ redness of swelling is present in the painful area
■ any new symptoms appear
You may report side effects to FDA at 1-800-FDA-1088

PREGNANCY

If pregnant or breast-feeding, ask a health professional before use. It is especially important not to use naproxen sodium during the last 3 months of pregnancy unless definitely directed to do so by a doctor because it may cause problems in the unborn child or complications during delivery.

KEEP OUT OF REACH OF CHILDREN

In case of overdose, get medical help or contact a Poison Control Center right away.

DIRECTIONS

Adults and children 12 years and over

■ take 1 tablet every 8 to 12 hours while symptoms last

■ for the first dose you may take 2 tablets within the first hour
■ do not exceed 2 tablets in any 8 to 12 hour period
■ do not exceed 3 tablets in a 24 hr period

Children under 12 years

■ ask a doctor

OTHER INFORMATION

■ each tablet contains: sodium 20mg
■ store at 20 to 250C (68 to 770F). Avoid high
humidity and excessive heat above 400C (1040F).

INACTIVE INGREDIENTS

Polyvinyl Pyrolidone, Microcrystalline Cellulose, Starch 1500, Sodium Starch Glycolate, Talc, Magnesium Stearate, FD&C Blue #2, Purified Water, Polysorbate 80, Titanium Dioxide, Polyethylene Glycol, Hypromellose

QUESTIONS OR COMMENTS?

Call 1-732-698-5070 Monday through Friday 9AM–5PM EST or www.pioneerlifesciences.com

Do not Use:

■ if you have ever had an allergic reaction to
any other pain reliever/fever reducer
■ right before or after heart surgery

When using this product

■ take with food or milk if stomach upset occurs